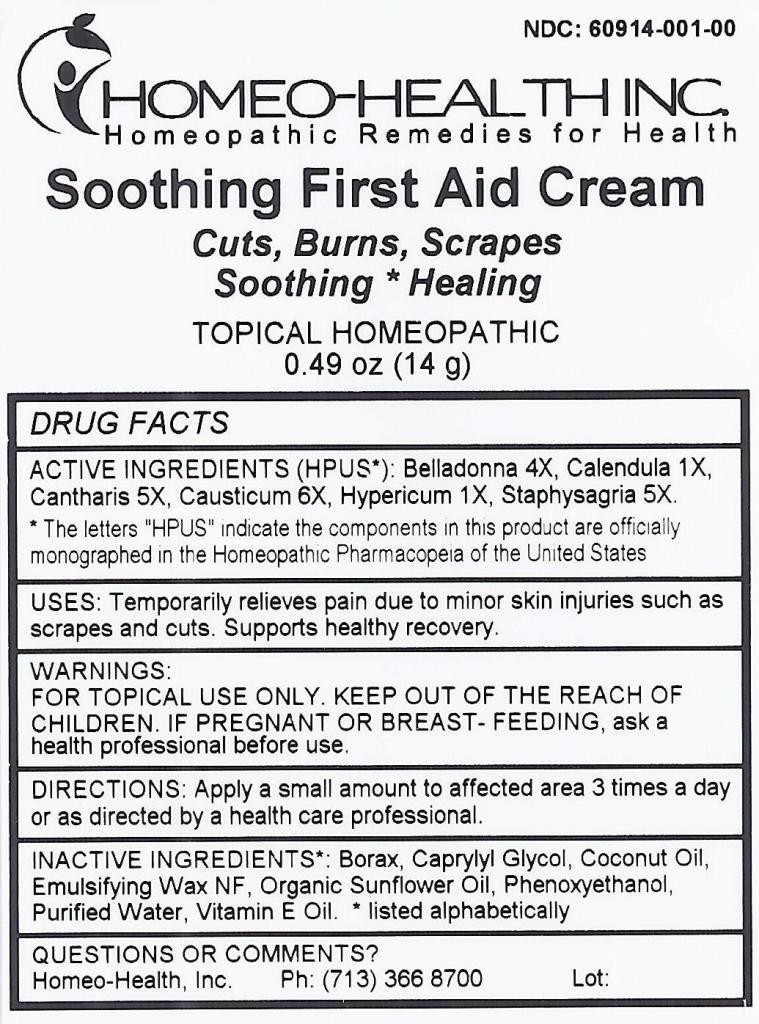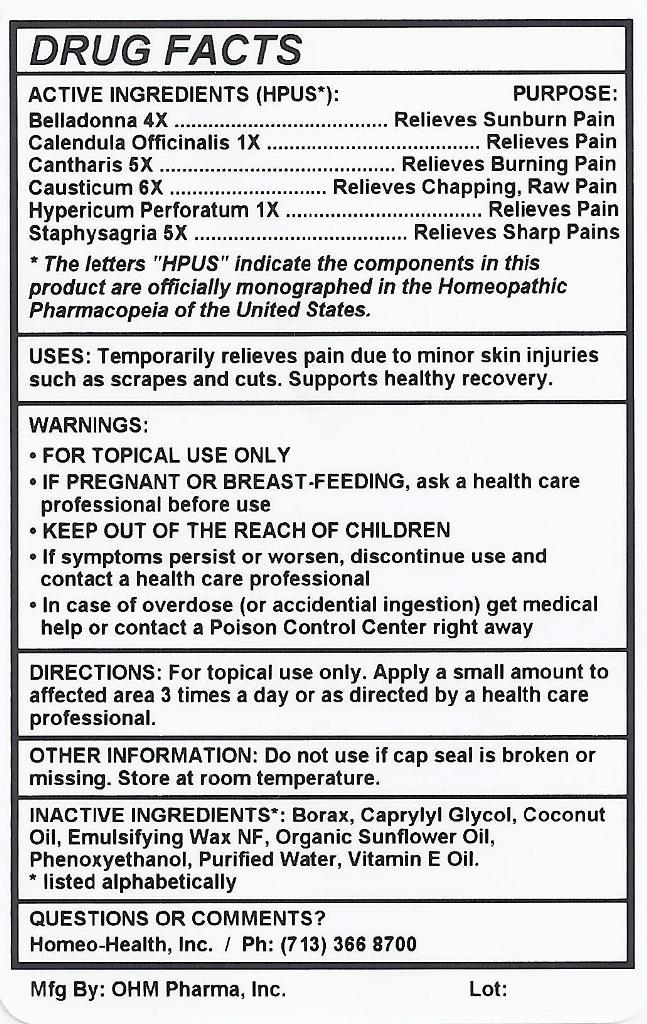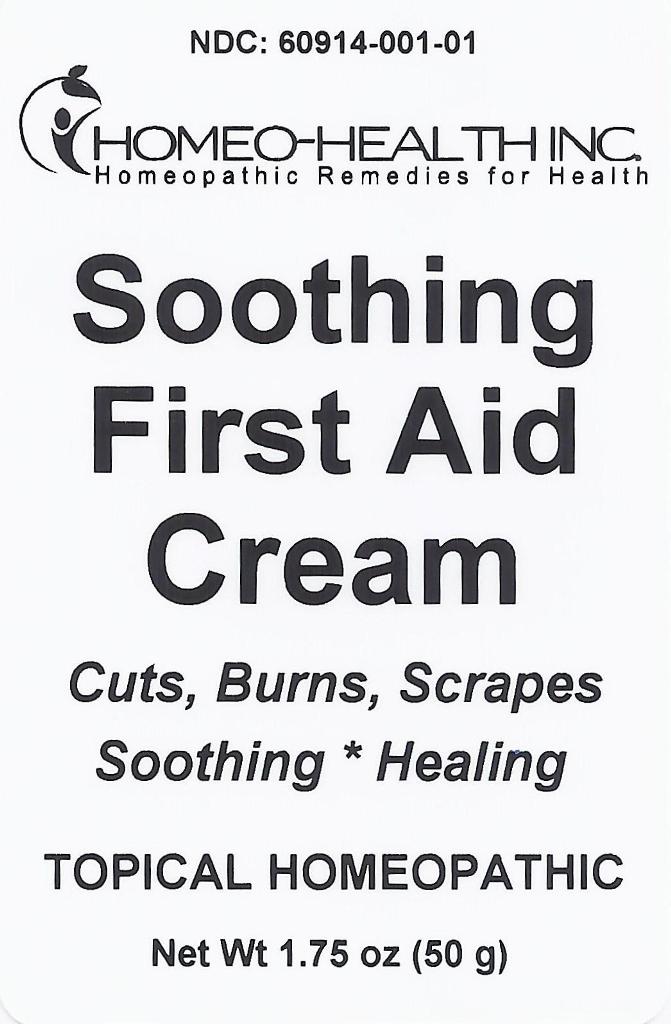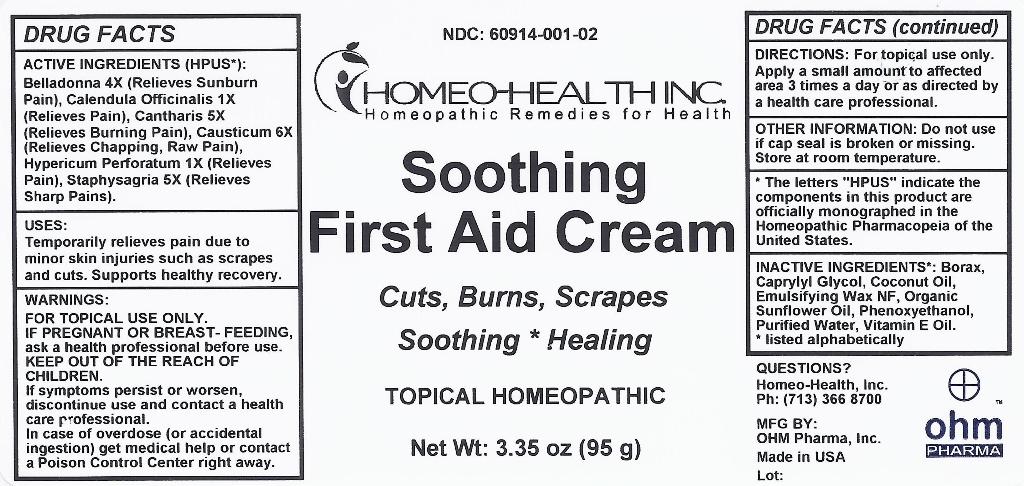 DRUG LABEL: Soothing First Aid Cream
NDC: 60914-001 | Form: CREAM
Manufacturer: Homeo Health, Inc.
Category: homeopathic | Type: HUMAN OTC DRUG LABEL
Date: 20190905

ACTIVE INGREDIENTS: ATROPA BELLADONNA 4 [hp_X]/1 g; CALENDULA OFFICINALIS FLOWERING TOP 1 [hp_X]/1 g; LYTTA VESICATORIA 5 [hp_X]/1 g; CAUSTICUM 6 [hp_X]/1 g; HYPERICUM PERFORATUM 1 [hp_X]/1 g; DELPHINIUM STAPHISAGRIA SEED 5 [hp_X]/1 g
INACTIVE INGREDIENTS: SODIUM BORATE; CAPRYLYL GLYCOL; COCONUT OIL; POLYSORBATE 60; SUNFLOWER OIL; PHENOXYETHANOL; WATER; .ALPHA.-TOCOPHEROL

Soothing First Aid Cream

ACTIVE INGREDIENTS

Active Ingredients (HPUS*): | Purpose:
Belladonna 4X | Relieves Sunburn Pain
Calendula Officinalis 1X | Relieves Pain
Cantharis 5X | Relieves Burning Pain
Causticum 6X | Relieves Chapping, Raw Pain
Hypericum Perforatum 1X | Relieves Pain
Staphysagria 5X | Relieves Sharp Pains

USES

Uses: Temporarily relieves pain due to minor skin injuries such as scrapes and cuts. Supports healthy recovery.

WARNINGS

- For topical use only
- If pregnant or breast-feeding, ask a health care professional before use
- Keep out of the reach of children
- If symptoms persist or worsen, discontinue use and contact a health care professional
- In case of overdose (or accidental ingestion) get medical help or contact a Poison Control Center right away.

Keep out of the reach of children.

DIRECTIONS

Directions: For topical use only. Apply a small amount to affected area 3 times a day or as directed by a health care professional.

OTHER INFORMATION

Other Information: Do not use if cap seal is broken or missing. Store at room temperature.

INACTIVE INGREDIENTS

Inactive Ingredients*: Borax, Caprylyl Glycol, Coconut Oil, Emulsifying Wax NF, Organic Sunflower Oil, Phenoxyethanol, Purified Water, Vitamin E Oil.

* listed alphabetically

QUESTIONS OR COMMENTS?

Homeo-Health, Inc.

Ph: (713) 366 8700

Mfg By:

OHM Pharma, Inc.

Made in USA

PACKAGE LABEL

NDC: 60914-001-00

NDC: 60914-001-01

NDC: 60914-001-02

HOMEO-HEALTH INC.

Homeopathic Remedies for Health

SOOTHING FIRST AID CREAM

Cuts, Burns, Scrapes

Soothing * Healing

TOPICAL HOMEOPATHIC

Net Wt: 0.49 oz (14 g)

Net Wt: 1.75 oz (50 g)

Net Wt: 3.35 oz (95 g)

PURPOSE

Cuts, Burns, Scrapes

Soothing * Healing